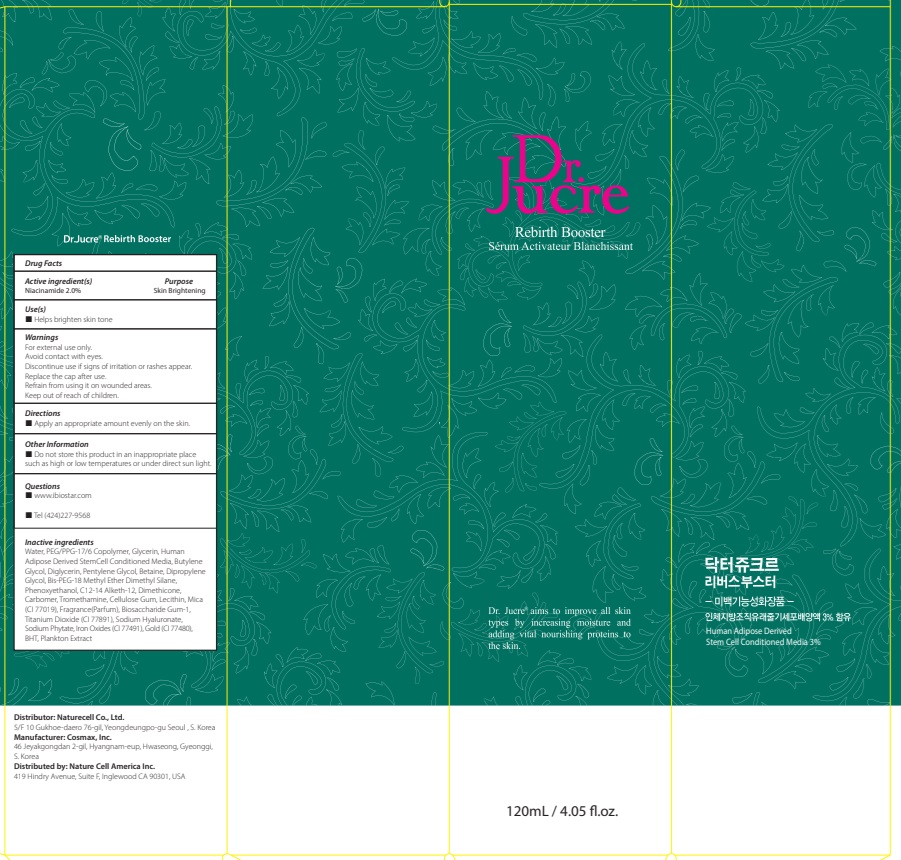 DRUG LABEL: Dr.Jucre Rebirth Booster
NDC: 83071-110 | Form: LIQUID
Manufacturer: NATURECELL CO., LTD.
Category: otc | Type: HUMAN OTC DRUG LABEL
Date: 20250102

ACTIVE INGREDIENTS: NIACINAMIDE 2 g/100 mL
INACTIVE INGREDIENTS: WATER; PEG/PPG-17/6 COPOLYMER; GLYCERIN

ACTIVE INGREDIENTS

Niacinamide 2.0%

INACTIVE INGREDIENTS

Water, PEG/PPG-17/6 Copolymer, Glycerin, Human Adipose Derived Stem Cell Conditioned Media, Butylene Glycol, Diglycerin, Pentylene Glycol, Betaine, Dipropylene Glycol, Bis-PEG-18 Methyl Ether Dimethyl Silane, Phenoxyethanol, C12-14 Alketh-12, Dimethicone, Carbomer, Tromethamine, Cellulose Gum, Lecithin, Mica (CI 77019), Fragrance(Parfum), Biosaccharide Gum-1, Titanium Dioxide (CI 77891), Sodium Hyaluronate, Sodium Phytate, Iron Oxides (CI 77491), Gold (CI 77480), BHT, Plankton Extract

PURPOSE

Skin Brightening

WARNINGS

For external use only.
Avoid contact with eyes.
Discontinue use if signs of irritation or rashes appear.
Replace the cap after use.
Refrain from using it on wounded areas.
Keep out of reach of children.

KEEP OUT OF REACH OF CHILDREN

Keep out of the reach of children.

Uses

■ Helps brighten skin tone

Directions

■ Apply an appropriate amount evenly on the skin.

Other Information

■ Do not store this product in an inappropriate place such as high or low temperatures or under direct sun light.

Questions

■ www.ibiostar.com
■ Tel (424)227-9568